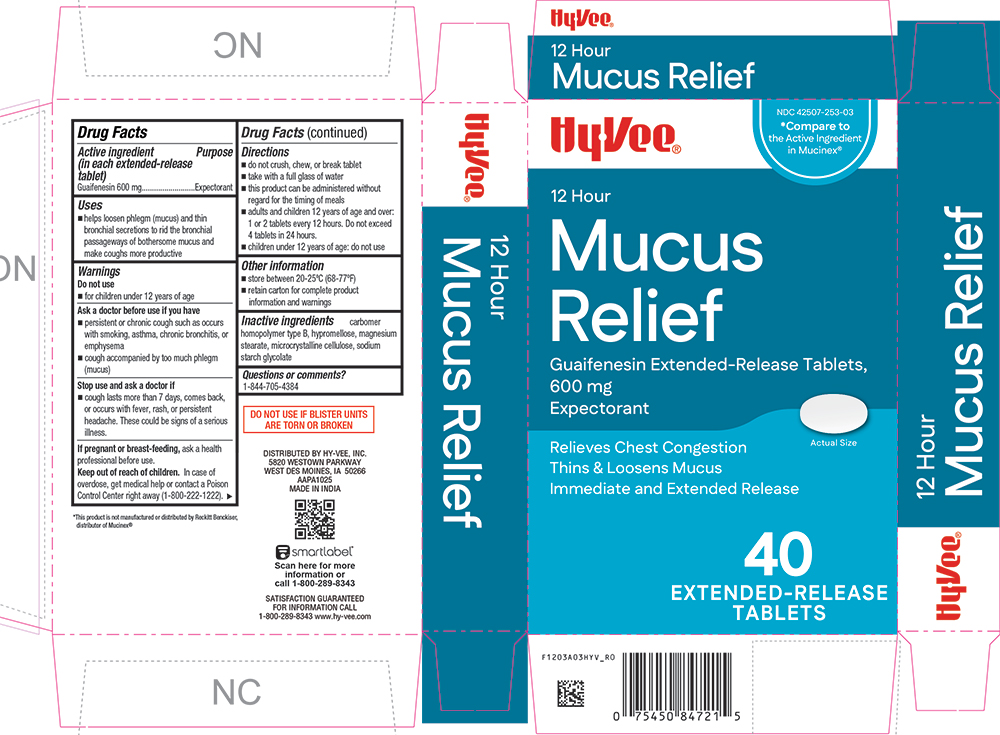 DRUG LABEL: Mucus Relief
NDC: 42507-253 | Form: TABLET, EXTENDED RELEASE
Manufacturer: HYVEE INC
Category: otc | Type: HUMAN OTC DRUG LABEL
Date: 20260113

ACTIVE INGREDIENTS: GUAIFENESIN 600 mg/1 1
INACTIVE INGREDIENTS: CARBOMER HOMOPOLYMER TYPE B (ALLYL SUCROSE CROSSLINKED); HYPROMELLOSE 2910 (15 MPA.S); SODIUM STARCH GLYCOLATE TYPE A; MAGNESIUM STEARATE; MICROCRYSTALLINE CELLULOSE

1203A-HYV-2026-0113

Drug Facts

Active ingredient (in each extended-release tablet)

Guaifenesin 600 mg

Purpose

Expectorant

Uses

■ helps loosen phlegm (mucus) and thin bronchial secretions to rid the bronchial passageways of bothersome mucus and make coughs more productive

Warnings

Do not use

■ for children under 12 years of age

Ask a doctor before use if you have

■ persistent or chronic cough such as occurs with smoking, asthma, chronic bronchitis, or emphysema

■ cough accompanied by too much phlegm (mucus)

Stop use and ask a doctor if

■ cough lasts more than 7 days, comes back, or occurs with fever, rash, or persistent headache. These could be signs of a serious illness.

PREGNANCY OR BREAST FEEDING

If pregnant or breast-feeding, ask a health professional before use.

Keep out of reach of children.In case of overdose, get medical help or contact a Poison Control Center right away (1-800-222-1222).

Directions

■ do not crush, chew, or break tablet

■ take with a full glass of water

■ this product can be administered without regard for the timing of meals

■ adults and children 12 years of age and over: 1 or 2 tablets every 12 hours. Do not exceed 4 tablets in 24 hours.

■ children under 12 years of age: do not use

Other information

■ store between 20-25ºC (68-77ºF)

■ retain carton for complete product information and warnings

Inactive ingredients

carbomer homopolymer type B, hypromellose, magnesium stearate, microcrystalline cellulose, sodium starch glycolate

Questions or comments?

1-844-705-4384

PRINCIPAL DISPLAY PANEL

HyVee®

NDC 42507-253-03

*Compare to the Active Ingredient in Mucinex®

12 Hour

Mucus Relief

Guaifenesin Extended-Release Tablets, 600 mg

Expectorant

Relieves Chest Congestion

Thins & Loosens Mucus

Immediate and Extended-Release

Actual Size

40 EXTENDED-RELEASE TABLETS